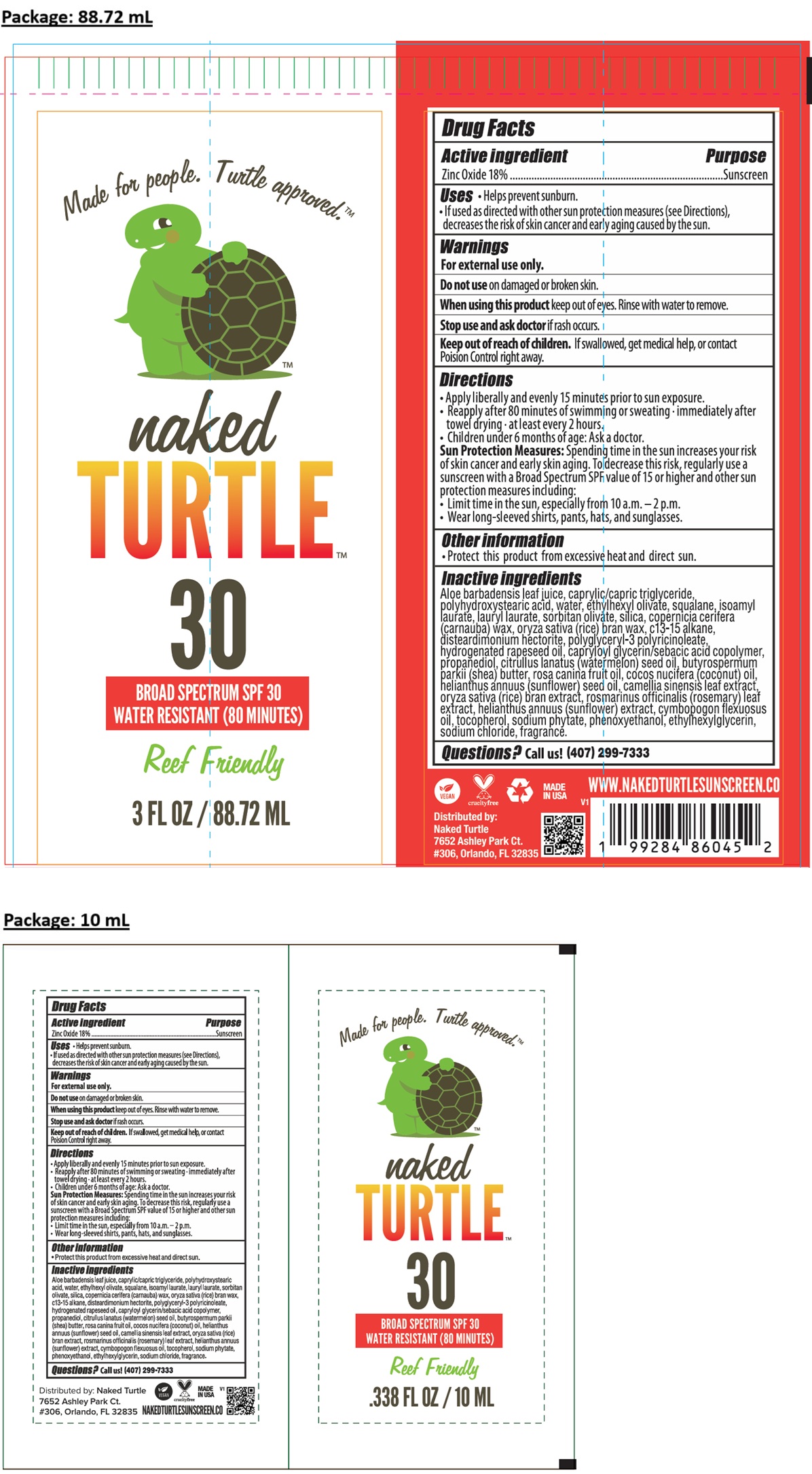 DRUG LABEL: naked TURTLE 30
NDC: 87058-001 | Form: LOTION
Manufacturer: NAKED TURTLE SUNSCREEN LLC
Category: otc | Type: HUMAN OTC DRUG LABEL
Date: 20250826

ACTIVE INGREDIENTS: ZINC OXIDE 18 g/100 mL
INACTIVE INGREDIENTS: ALOE VERA LEAF JUICE; MEDIUM-CHAIN TRIGLYCERIDES; POLYHYDROXYSTEARIC ACID (2300 MW); WATER; ETHYLHEXYL OLIVATE; SQUALANE; ISOAMYL LAURATE; LAURYL LAURATE; SORBITAN OLIVATE; SILICON DIOXIDE; CARNAUBA WAX; RICE BRAN; C13-15 ALKANE; DISTEARDIMONIUM HECTORITE; POLYGLYCERYL-3 PENTARICINOLEATE; HYDROGENATED RAPESEED OIL; CAPRYLOYL GLYCERIN/SEBACIC ACID COPOLYMER (2000 MPA.S); PROPANEDIOL; WATERMELON SEED OIL; SHEA BUTTER; ROSA CANINA FRUIT OIL; COCONUT OIL; SUNFLOWER OIL; GREEN TEA LEAF; ROSEMARY; HELIANTHUS ANNUUS FLOWERING TOP; EAST INDIAN LEMONGRASS OIL; TOCOPHEROL; PHYTATE SODIUM; PHENOXYETHANOL; ETHYLHEXYLGLYCERIN; SODIUM CHLORIDE

naked TURTLE 30

Active ingredient

Zinc Oxide 18%

Purpose

Sunscreen

Uses

• Helps prevent sunburn.
• If used as directed with other sun protection measures (see Directions), decreases the risk of skin cancer and early aging caused by the sun.

Warnings

For external use only.

Do not use on damaged or broken skin.

When using this product keep out of eyes. Rinse with water to remove.

Stop use and ask doctor if rash occurs.

Keep out of reach of children. If swallowed, get medical help, or contact Poison Control right away.

Directions

• Apply liberally and evenly 15 minutes prior to sun exposure.
• Reapply after 80 minutes of swimming or sweating • immediately after towel drying • at least every 2 hours.
• Children under 6 months of age: Ask a doctor.
Sun Protection Measures: Spending time in the sun increases your risk of skin cancer and early skin aging. To decrease this risk, regularly use a sunscreen with a Broad Spectrum SPF value of 15 or higher and other sun protection measures including:
• Limit time in the sun, especially from 10 a.m. - 2 p.m.
• Wear long-sleeved shirts, pants, hats, and sunglasses.

Other information

• Protect his product from excessive heat and direct sun.

Inactive ingredients

Aloe barbadensis leaf juice, caprylic/capric triglyceride, polyhydroxystearic acid, water, ethylhexyl olivate, squalane, isoamyl laurate, lauryl laurate, sorbitan olivate, silica, copernicia cerifera (carnauba) wax, oryza sativa (rice) bran wax, c13-15 alkane, disteardimonium hectorite, polyglyceryl-3 polyricinoleate, hydrogenated rapeseed oil, capryloyl glycerin/sebacic acid copolymer, propanediol, citrullus lanatus (watermelon) seed oil, butyrospermum parkii (shea) butter, rosa canina fruit oil, cocos nucifera (coconut) oil, helianthus annuus (sunflower) seed oil, camellia sinensis leaf extract, oryza sativa (rice) bran extract, rosmarinus officinalis (rosemary) leaf extract, helianthus annuus (sunflower) extract, cymbopogon flexuosus oil, tocopherol, sodium phytate, phenoxyethanol, ethylhexylglycerin, sodium chloride, fragrance.

Questions?

Call us! (407) 299-7333

Made for people. Turtle approved.TM

BROAD SPECTRUM SPF 30

WATER RESISTANT (80 MINUTES)

Reef Friendly

VEGAN crueltyfree MADE IN USA

Distributed by:
Naked Turtle
7652 Ashley Park Ct.
#306, Orlando, FL 32835

WWW.NAKEDTURTLESUNSCREEN.CO